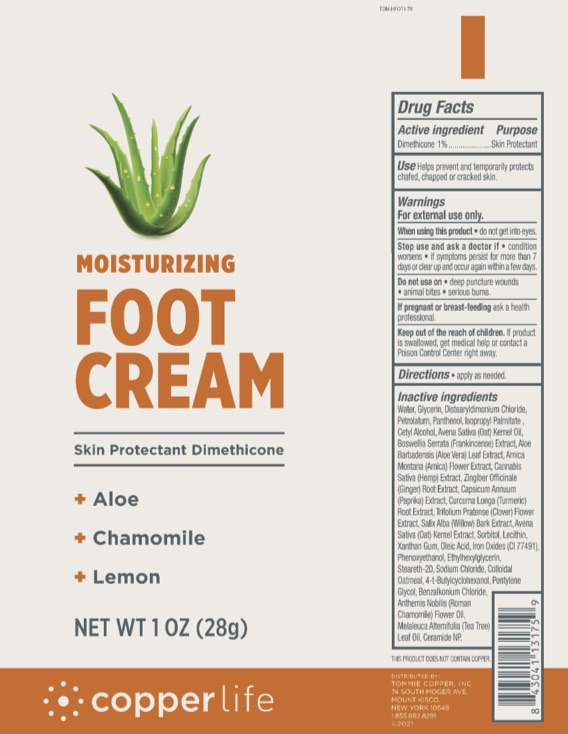 DRUG LABEL: Copperlife  Foot
NDC: 72562-211 | Form: CREAM
Manufacturer: Tommie Copper, Inc.
Category: otc | Type: HUMAN OTC DRUG LABEL
Date: 20241215

ACTIVE INGREDIENTS: DIMETHICONE 1 g/100 g
INACTIVE INGREDIENTS: LECITHIN, SOYBEAN; XANTHAN GUM; OATMEAL; BENZALKONIUM CHLORIDE; 4-TERT-BUTYLCYCLOHEXANOL; PENTYLENE GLYCOL; ETHYLHEXYLGLYCERIN; CERAMIDE NP; STEARETH-20; PETROLATUM; PAPRIKA; GREEN TEA LEAF; GINGER; FERRIC OXIDE RED; CALENDULA OFFICINALIS FLOWER; WATER; OLEIC ACID; STEARIC ACID; GLYCERIN; ALOE VERA LEAF; TURMERIC; TEA TREE OIL; CETYL ALCOHOL; ARNICA MONTANA FLOWER; FRANKINCENSE; CANNABIS SATIVA FLOWERING TOP; PHENOXYETHANOL; SODIUM CHLORIDE; ISOPROPYL PALMITATE; OAT KERNEL OIL; OAT; SORBITOL; PANTHENOL; DISTEARYLDIMONIUM CHLORIDE; TRIFOLIUM PRATENSE FLOWER; WILLOW BARK; CHAMAEMELUM NOBILE FLOWER OIL

Copperlife Foot Cream

ACTIVE INGREDIENT

Dimethicone 1%

PURPOSE

Skin Protectant

INDICATIONS AND USAGE

Helps prevent and temporarily protects chafed, chapped, or cracked skin.

WARNINGS

For external use only. When using this product do not get into eyes. Stop use and ask a doctor if condition worsens, if symptoms persist for more than 7 days or clear up and occur again within a few days. Do not use on deep puncture wounds, animal bites, and serious burns.

PREGNANCY OR BREAST FEEDING

If pregnant or breast-feeding ask a health professional.

KEEP OUT OF REACH OF CHILDREN

If swallowed, get medical help or contact a Poison Control Center right away.

DOSAGE AND ADMINISTRATION

Apply as needed.

INACTIVE INGREDIENT

Water, Glycerin, Distearyldimonium Chloride, Petrolatum, Panthenol, Isopropyl Palmitate, Cetyl Alcohol, Avena Sativa (Oat) Kernel Oil, Boswellia Serrata (Frankincense) Extract, Arnica Montana (Arnica) Flower Extract, Cannabis Sativa (Hemp) Extract, Zingiber Officinale (Ginger) Root Extract, Capsicum Annuum (Paprika) Extract, Curcuma Longa (Tumeric) Root Extract, Trifolium Pratense (Clover) Flower Extract, Salix Alba (Willow) Bark Extract, Avena Sativa (Oat) Kernel Extract, Sorbitol, Lecithin, Xanthan Gum, Oleic Acid, Iron Oxides (CI 77491), Phenoxyethanol, Ethylhexylglycerin, Steareth-20, Sodium Chloride, Colloidal Oatmeal, 4-t-Butylcyclohexanol, Pentylene Glycol, Benzalkonium Chloride, Anthemis Nobilis (Roman Chamomile) Flower Oil, Melaleuca Altrnifolia (Tea Tree) Leaf Oil, Ceramide NP.